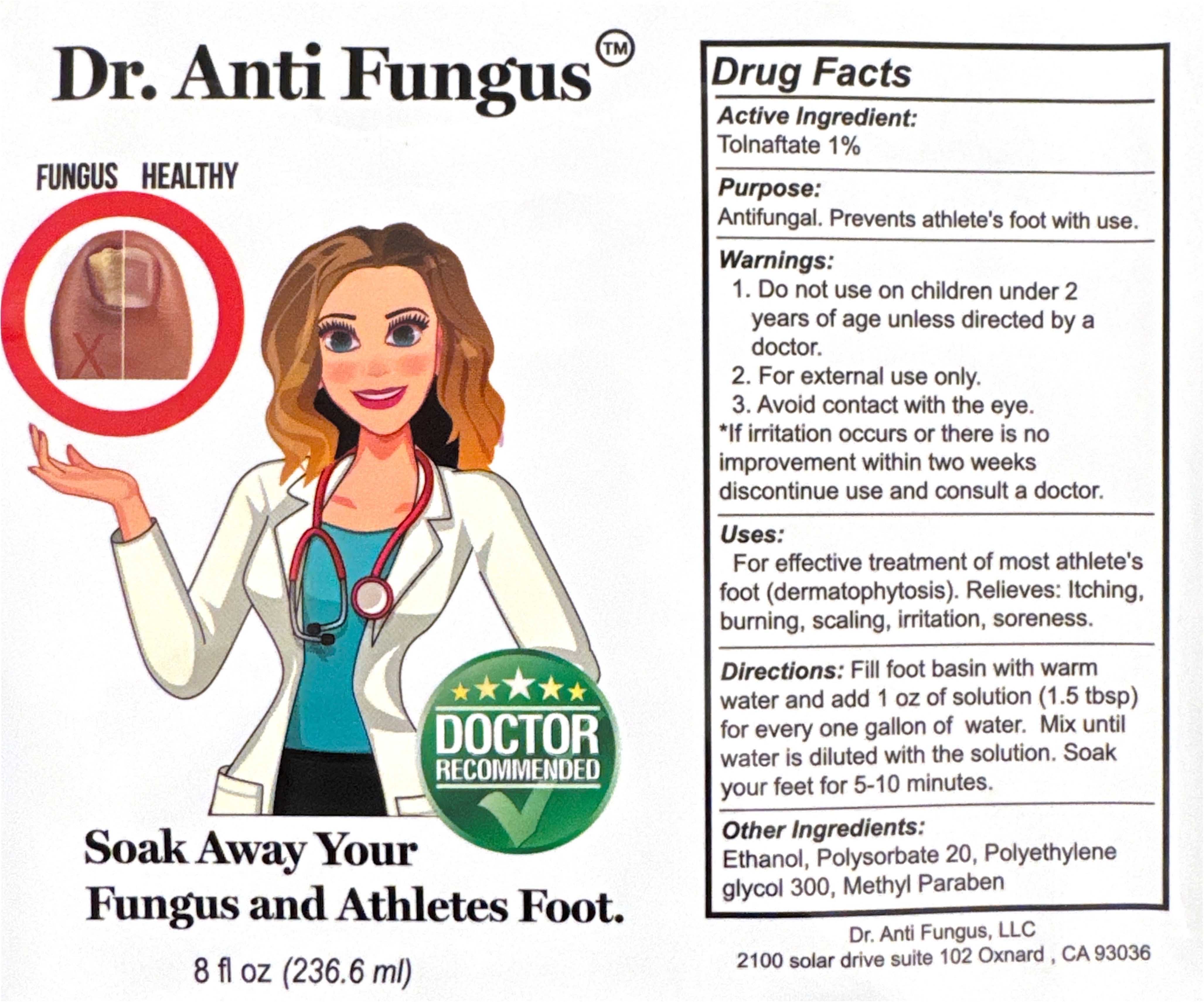 DRUG LABEL: Dr. Anti Fungus
NDC: 65112-300 | Form: SOLUTION
Manufacturer: I. Shay Cosmetics
Category: otc | Type: HUMAN OTC DRUG LABEL
Date: 20241113

ACTIVE INGREDIENTS: TOLNAFTATE 0.01 mg/236.6 mL
INACTIVE INGREDIENTS: METHYLPARABEN 0.2 mg/236.6 mL

ACTIVE INGREDIENT

Tolnaftate 1%

PURPOSE

Antifungal. Prevents athlete's foot with use.

INDICATIONS AND USAGE

For effective treatment of most athlete's foot (dermatophytosis). Relieves: Itching, burning, scaling, irritation, soreness.

INACTIVE INGREDIENT

Ethanol, Polysorbate 20, Polyethylene Glycol 300, Methylparaben.

WARNINGS

1. Do not use on children under 2 years of age unless directed by a doctor.

2. For external use only.

3. Avoid contact with the eye.

* If irritation occurs or there is no improvement within two weeks discontinue use and consult a doctor.

DOSAGE AND ADMINISTRATION

Fill foot basin with warm water and add 1 oz of solution (1.5 tbsp) for every one gallon of water. Mix until water is diluted with the solution. Soak your feet for 5-10 minutes.

WARNINGS - Keep children out of reach.